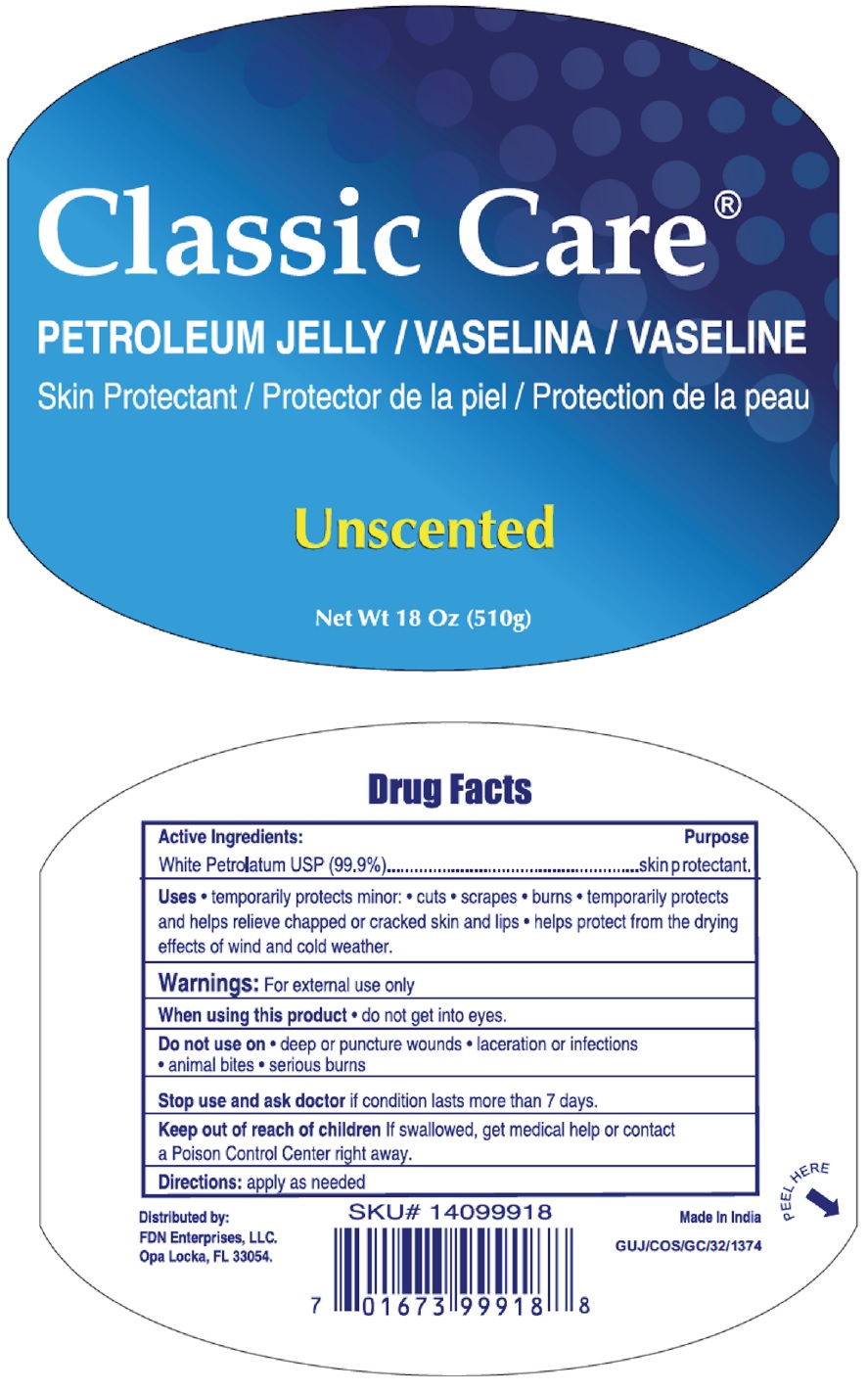 DRUG LABEL: Classic Care Petroleum
NDC: 60691-130 | Form: JELLY
Manufacturer: FDN Enterprises, LLC
Category: otc | Type: HUMAN OTC DRUG LABEL
Date: 20210915

ACTIVE INGREDIENTS: PETROLATUM 99.9 g/100 g
INACTIVE INGREDIENTS: WATER

Classic Care® Petroleum Jelly

Active Ingredients

White Petrolatum USP (99.9%)

Purpose

skin protectant

Uses

• temporarily protects minor: • cuts • scrapes • burns • temporarily protects and helps relieve chapped or cracked skin and lips • helps protect from the drying effects of wind and cold weather.

Warnings

For external use only

When using this product • do not get into eyes.

Do not use on • deep or puncture wounds • laceration or infections • animal bites • serious burns

Stop use and ask doctor if condition lasts more than 7 days.

Keep out of reach of children If swallowed, get medical help or contact a Poison Control Center right away.

Directions:

apply as needed

Inactive ingredients

Water

PETROLEUM JELLY/ VASELINE

Unscented

Distributed by:

FDN Enterprises, LLC.

Opa Locka, FL 33054.

Made In India